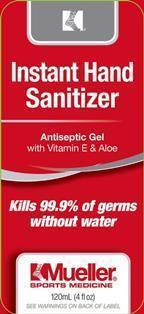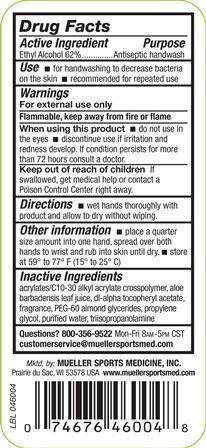 DRUG LABEL: Mueller Instant Hand Sanitizer
NDC: 52564-460 | Form: LIQUID
Manufacturer: Mueller Sports Medicine, Inc.
Category: otc | Type: HUMAN OTC DRUG LABEL
Date: 20141211

ACTIVE INGREDIENTS: ALCOHOL 62 mL/100 mL
INACTIVE INGREDIENTS: CARBOMER INTERPOLYMER TYPE A (ALLYL SUCROSE CROSSLINKED); ALOE VERA LEAF; .ALPHA.-TOCOPHEROL ACETATE, DL-; PEG-60 ALMOND GLYCERIDES; PROPYLENE GLYCOL; WATER; TRIISOPROPANOLAMINE

PACKAGE LABEL

ACTIVE INGREDIENT

Ethyl Alcohol 62%

PURPOSE

Antiseptic handwash

Keep out of reach of children. If swallowed, get medical help or contact a Poison Control Center right away.

INDICATIONS AND USAGE

Use for handwashing to decrease bacteria on the skin. recommended for repeated use

WARNINGS

For external use only, Flammable, keep away from fire or flame. When using this product do no tuse in the eyes. discontinue use if irritation and redness develop. If condition persists for more than 72 hours consult a doctor.

DOSAGE AND ADMINISTRATION

Directions. Wer hands thoroughly with product and allow to dry without wiping.

Other information. place a quarter size amount into one hand, spread over both hands to wrist and rub into skin until dry. Store at 59 to 77 degrees Farenheit (15 to 25 degrees Celsius)

INACTIVE INGREDIENT

Acrylates/C10-30 alkyl acrylate crosspolymer, aloe barbadensis leaf juice, dl-alpha tocopheryl acetate, fragrance, PEG-60 almond glycerides, propylene glycol, purified water, triisopropanolamine